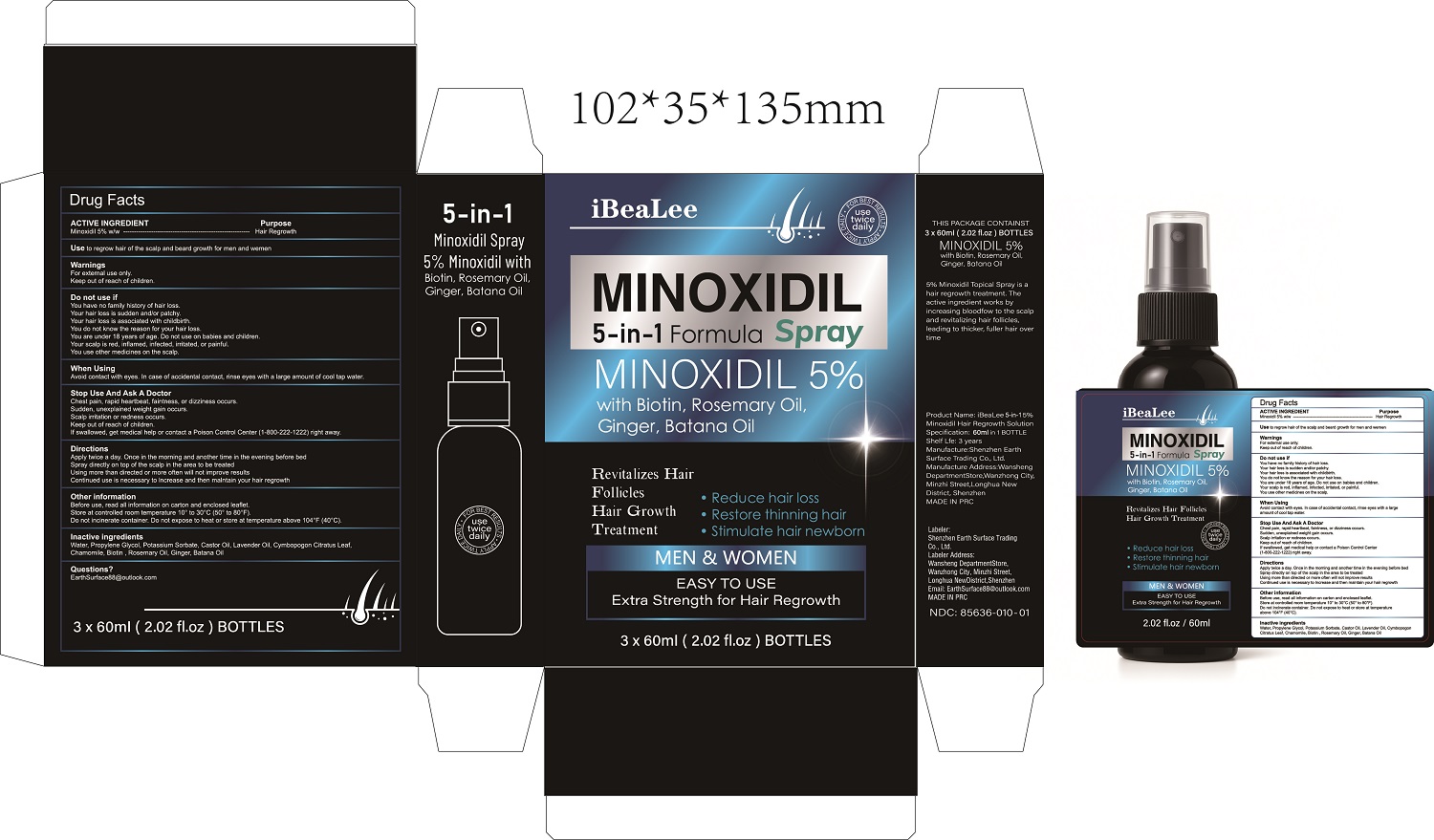 DRUG LABEL: iBeaLee 5-in-1 5% Minoxidil Hair Regrowth Solution
NDC: 85636-010 | Form: SPRAY
Manufacturer: Shenzhen Earth Surface Trading Co., Ltd.
Category: otc | Type: HUMAN OTC DRUG LABEL
Date: 20251127

ACTIVE INGREDIENTS: MINOXIDIL 5 g/100 mL
INACTIVE INGREDIENTS: PROPYLENE GLYCOL; POTASSIUM SORBATE; CASTOR OIL; WATER; CHAMOMILE; CYMBOPOGON CITRATUS LEAF; ROSEMARY; BIOTIN; LAVENDER OIL; GINGER

ACTIVE INGREDIENT

Minoxidil 5% w/w

Purpose

Hair Regrowth

Use

Use to regrow hair of the scalp and beard growth for men and wemen

Warnings

For external use only.
Keep out of reach of children.

Do not use if

You have no family history of hair loss.
Your hair loss is sudden and/or patchy.
Your hair loss is associated with childbirth.
You do not know the reason for your hair loss.
You are under 18 years of age. Do not use on babies and children.
Your scalp is red, inflamed, infected, irritated, or painful.
You use other medicines on the scalp.

When Using

Avoid contact with eyes. In case of accidental contact, rinse eyes with a large amount of cool tap water.

Stop Use And Ask A Doctor

Chest pain, rapid heartbeat, faintness, or dizziness occurs.
Sudden, unexplained weight gain occurs.
Scalp irritation or redness occurs.
Keep out of reach of children.
If swallowed, get medical help or contact a Poison Control Center (1-800-222-1222) right away.

Keep Out Of Reach Of Children

Directions

Apply twice a day. Once in the morning and another time in the
evening before bed
Spray directly on top of the scalp in the area to be treated
Using more than directed or more often will not improve results
Continued use is necessary to lncrease and then malntain your
hair regrowth

Other information

Before use, read all information on carton and enclosed leaflet.
Store at controlled room temperature 10° to 30°C (50° to 80°F).
Do not incinerate container. Do not expose to heat or store at temperature above 104°F (40°C).

Inactive ingredients

Water, Propylene Glycol, Potassium Sorbate, Castor Oil, Lavender Oil, Cymbopogon Citratus Leaf, Chamomile, Biotin , Rosemary Oil, Ginger, Batana Oil